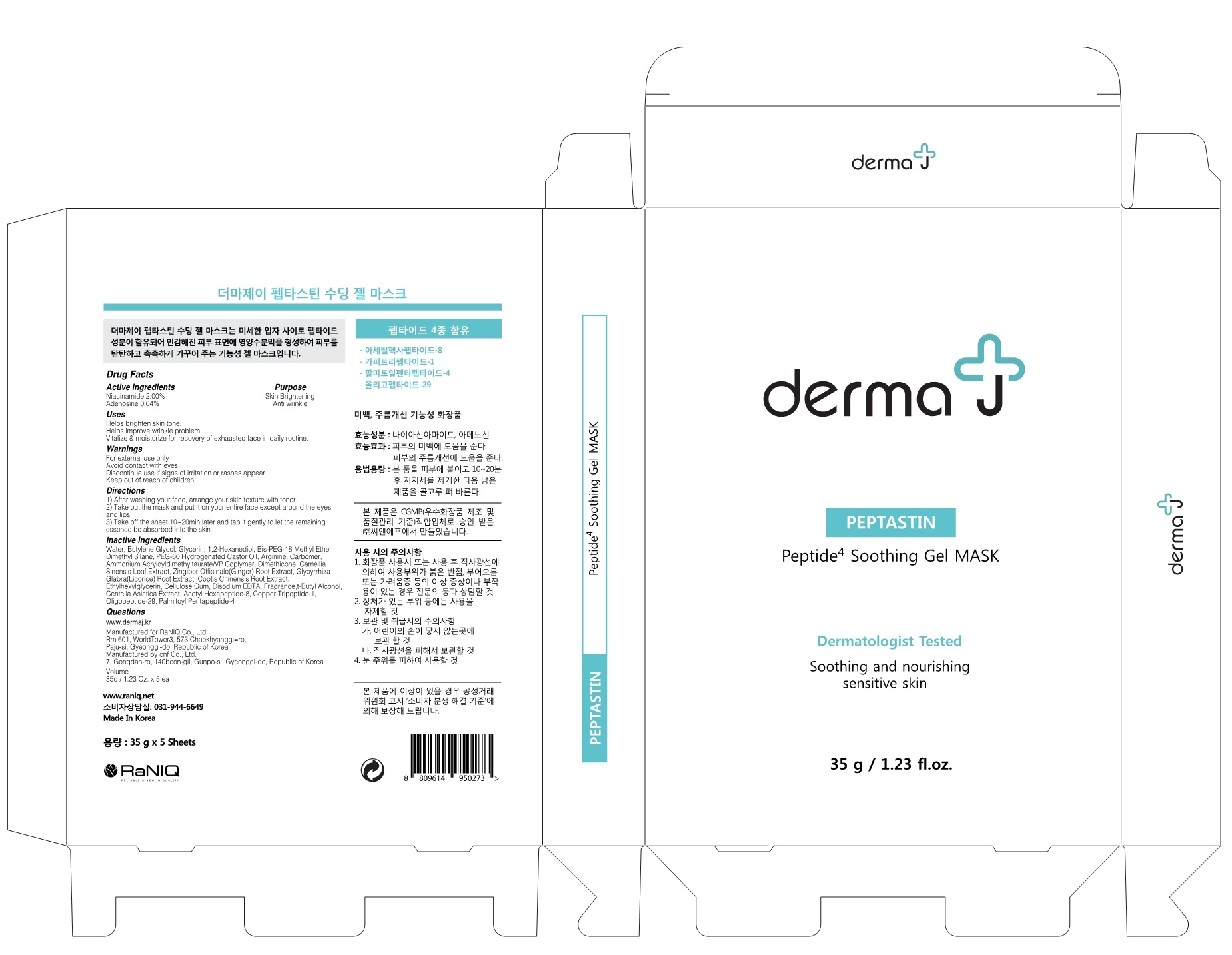 DRUG LABEL: derma J PEPTASTIN SOOTHING GEL MASK
NDC: 73225-010 | Form: PATCH
Manufacturer: Raniq. Co., Ltd
Category: otc | Type: HUMAN OTC DRUG LABEL
Date: 20190715

ACTIVE INGREDIENTS: Niacinamide 0.7 g/35 g; Adenosine 0.014 g/35 g
INACTIVE INGREDIENTS: Water; Butylene Glycol

ACTIVE INGREDIENT

Active ingredients: Niacinamide 2.00%, Adenosine 0.04%

INACTIVE INGREDIENT

Inactive ingredients:

Water, Butylene Glycol, Glycerin, 1,2-Hexanediol, Bis-PEG-18 Methyl Ether Dimethyl Silane, PEG-60 Hydrogenated Castor Oil, Arginine, Carbomer, Ammonium Acryloyldimethyltaurate/VP Coplymer, Dimethicone, Camellia Sinensis Leaf Extract, Zingiber Officinale(Ginger) Root Extract, Glycyrrhiza Glabra(Licorice) Root Extract, Coptis Chinensis Root Extract, Ethylhexylglycerin, Cellulose Gum, Disodium EDTA, Fragrance,t-Butyl Alcohol, Centella Asiatica Extract, Acetyl Hexapeptide-8, Copper Tripeptide-1, Oligopeptide-29, Palmitoyl Pentapeptide-4

PURPOSE

Purpose: Skin Brightening, Anti wrinkle

WARNINGS

For external use only
Avoid contact with eyes.
Discontinue use if signs of irritation or rashes appear.
Keep out of reach of children

KEEP OUT OF REACH OF CHILDREN SECTION

Uses

Helps brighten skin tone.
Helps improve wrinkle problem.
Vitalize & moisturize for recovery of exhausted face in daily routine.

Directions

1) After washing your face, arrange your skin texture with toner.
2) Take out the mask and put it on your entire face except around the eyes and lips.
3) Take off the sheet 10~20min later and tap it gently to let the remaining essence be absorbed into the skin

QUESTIONS

www.dermaj.kr